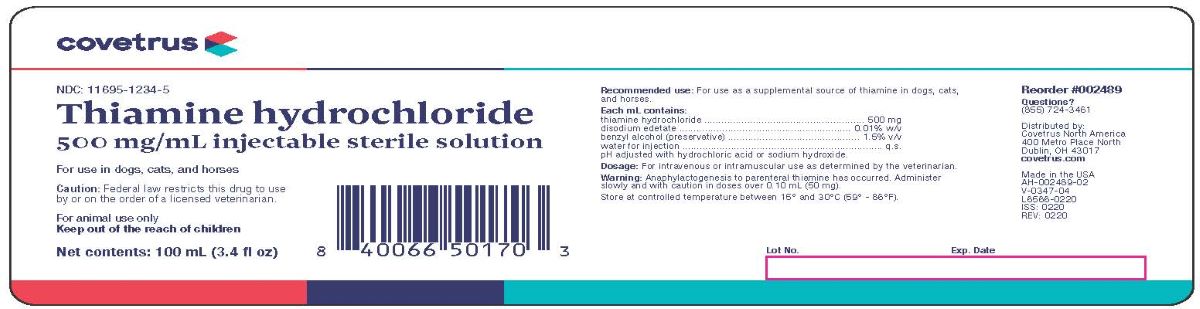 DRUG LABEL: Thiamine Hydrochloride
NDC: 11695-1234 | Form: INJECTION
Manufacturer: Covetrus North America
Category: animal | Type: PRESCRIPTION ANIMAL DRUG LABEL
Date: 20231212

ACTIVE INGREDIENTS: THIAMINE HYDROCHLORIDE 500 mg/1 mL
INACTIVE INGREDIENTS: EDETATE DISODIUM .1 mg/1 mL; BENZYL ALCOHOL .015 mL/1 mL; WATER

Thiamine Hydrochloride
500mg/mL Injectable Sterile Solution

Recommended Use:

For use as a supplemental source of thiamine in dogs, cats, and horses.

Each mL Contains:

Thiamine Hydrochloride..........................500 mg

Disodium Edetate..............................0.01% w/v

Benzyle Alcohol (as preservative)..........1.5% v/v

Water for Injection......................................q.s.

pH adjusted with Hydrochloric acid or Sodium Hydroxide

Dosage:

For intravenous or intramuscular use as determined by the veterinarian.

Warning:

Anaphylactogenesis to parental thiamine has occurred. Administer slowly and with caution in doses over 0.10 mL (50mg)

STORAGE AND HANDLING

Store at controlled temperatures between 15° and 30°C (59° - 86°F).

Reorder #002489

Questions?

(855) 724-346

Covetrus North America

400 Metro Place North

Dublin, OH 43017

covetrus.com

Made in the USA

AH-002489-02

V-0347-04

L6566-0220

ISS: 0220

REV: 0220

Principal Display Panel

THIAMINE HYDROCHLORIDE

500 mg/mL Injectable Sterile Solution

For use in dogs, cats and horses

Caution: Federal law restricts this drug to use by or on the order of a licensed veterinarian

FOR ANIMAL USE ONLY

KEEP OUT OF THE REACH OF CHILDREN

100 mL (3.4 fl oz)